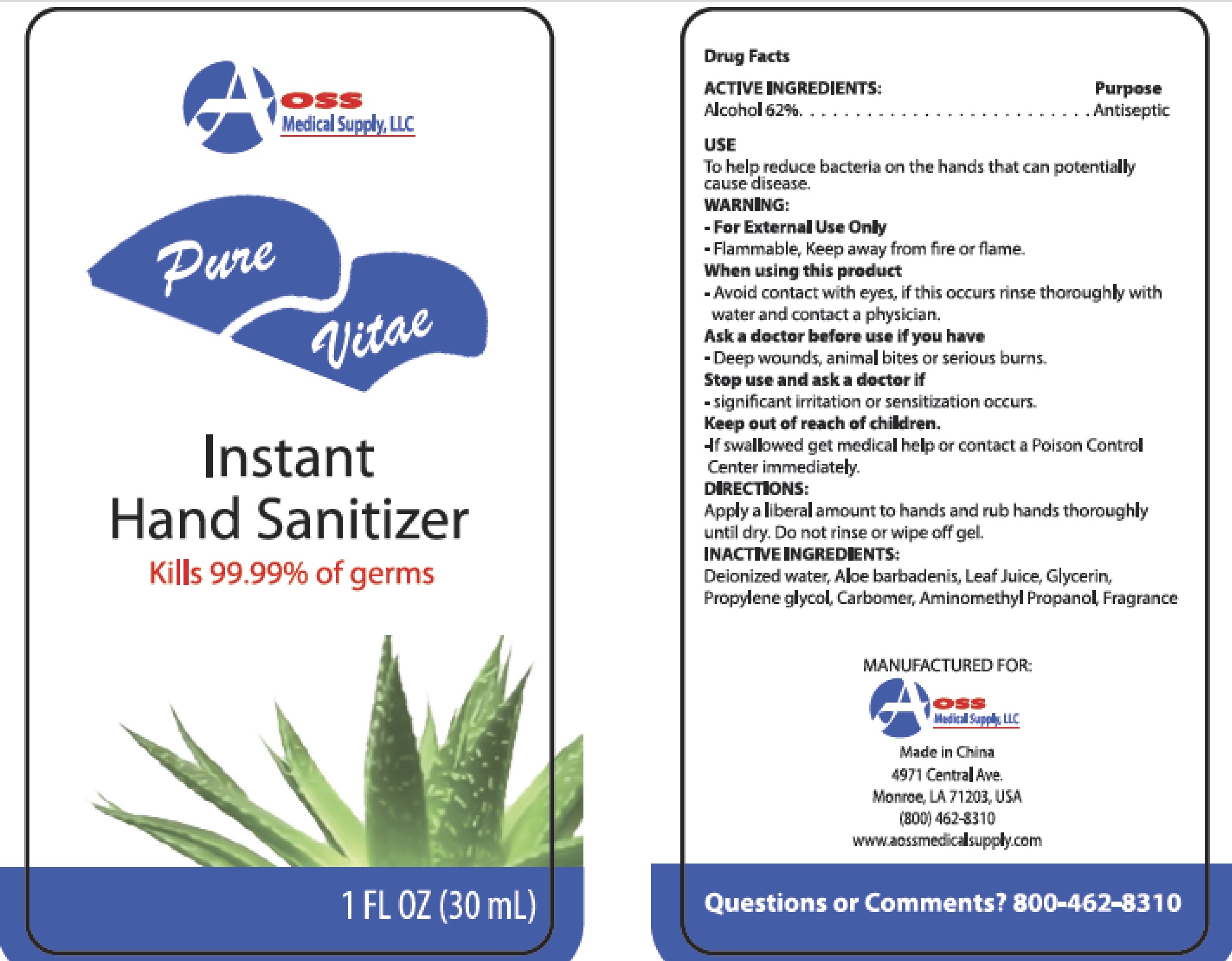 DRUG LABEL: Pure Vitac Instant Hand Sanitizer
NDC: 53152-0001 | Form: GEL
Manufacturer: AOSS Medical Supply, Inc.
Category: otc | Type: HUMAN OTC DRUG LABEL
Date: 20200905

ACTIVE INGREDIENTS: ALCOHOL 62 mL/100 mL
INACTIVE INGREDIENTS: CARBOMER COPOLYMER TYPE A (ALLYL PENTAERYTHRITOL CROSSLINKED); ALOE VERA LEAF; AMINOMETHYLPROPANOL; WATER; GLYCERIN; PROPYLENE GLYCOL

Pure Vitac Instant Hand Sanitizer

ACTIVE INGREDIENTS:

Alcohol 62%

Purpose

Antiseptic

USE

To help reduce bacteria on the hands that can potentially cause disease.

WARNING:

- For External Use Only
- Flammable, Keep away from fire or flame

When using this product

- Avoid contact with eyes, if this occurs rinse thoroughly with water and contact a physician

Ask a doctor before use if you have

- Deep wounds, animal bites or serious burns.

Stop use and ask a doctor if

- significant irritation or sensitization occurs

Keep out of reach of children

- If swallowed get medical help or contact a Poison Control Center immediately

DIRECTIONS:

Apply a liberal amount to hands and rub hands thoroughly until dry. Do not rinse or wipe off gel.

INACTIVE INGREDIENTS:

Deionized water, Aloe Barbadenis Leaf Juice, Glycerin, Propylene Glycol, Carbomer, Aminomethyl Propanol, Fragrance